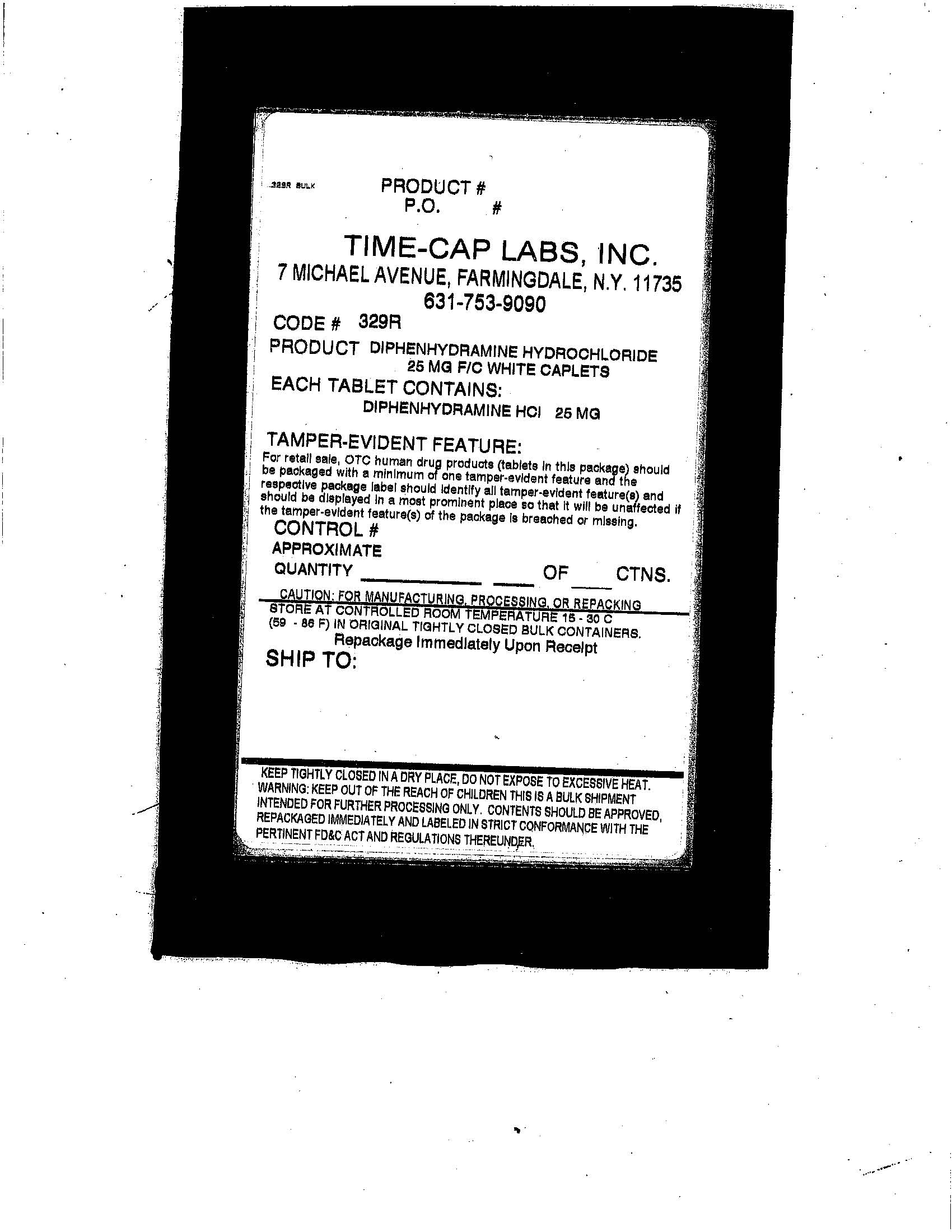 DRUG LABEL: DIPHENHYDRAMINE HYDROCHLORIDE
NDC: 49483-329 | Form: TABLET, COATED
Manufacturer: Time-Cap Labs, Inc
Category: otc | Type: HUMAN OTC DRUG LABEL
Date: 20181217

ACTIVE INGREDIENTS: DIPHENHYDRAMINE HYDROCHLORIDE 25 mg/1 1
INACTIVE INGREDIENTS: CARNAUBA WAX; SILICON DIOXIDE; CROSCARMELLOSE SODIUM	; DIBASIC CALCIUM PHOSPHATE DIHYDRATE; HYPROMELLOSES	; MAGNESIUM STEARATE; CELLULOSE, MICROCRYSTALLINE; POLYETHYLENE GLYCOL; POLYSORBATE 80; TITANIUM DIOXIDE

329R DIP HCL

Active Ingredient

(in each caplet)

Diphenhydramine Hcl 25 mg

Ask a doctor before use if you have

glaucoma;

trouble urinating due to an enlarged prostate gland;

a breathing problem such as emphysema or chronic bronchitis

Ask a doctor or pharmacist before use if you are taking sedatives or tranquilizers.

Do not use

to make a child sleepy; with any other product containing diphenhydramine, even one used on skin.

Keep out of reach of children. In case of overdose, get medical help or contact a Poison Control Center right away.

Warnings

Do not use to make a child sleepy; Do not use with any other product containing diphenhydramine even one used on skin.

PREGNANCY OR BREAST FEEDING

If pregnant or breast-feeding ask a health professional before use.

PURPOSE

Uses: temporarily relieves these symptoms due to hay fever or other upper respiratory allergies

runny nose; itchy water eyes sneezing;itchy nose or throat

Temporarily relieves these symptoms due to the common cold: runny nose; sneezing

When using this product

Avoid alcoholic drinks

marked drowsiness may occur

Alcohol, sedatives, and tranquilizers may increase drowsiness

Excitability may occur, especially in children

Be careful when driving a motor vehicle or operating machinery

Directions:

Take every 4 to 6 hours

Do not take more than 6 doses in 24 hours

Adults and children 12 years of age and over - 1 to 2 caplets

Children 6 to under 12 years of age - 1 caplet

Children under 6 years of age - Do not use this product in children under 6 years of age

INACTIVE INGREDIENT

Carnauba Wax, Colloidal Silicon Dioxide, Croscarmellose Sodium, Dibasic Calcium Phosphate Dihydrate, Hypromellose, Magnesium Stearate, Microcrystalline Cellulose, Polyethylene Glycol, Polysorbate 80, Titanium Dioxide

INDICATIONS AND USAGE

Uses: Temporarily relieves these symptoms due to hay fever or other upper respiratory allergies; runny nose, itchy watery eyes; sneezing; itchy nose or throat

Temporarily relieves these symptoms due to the common cold: runny nose; sneezing

PACKAGE LABEL

Enter section text here